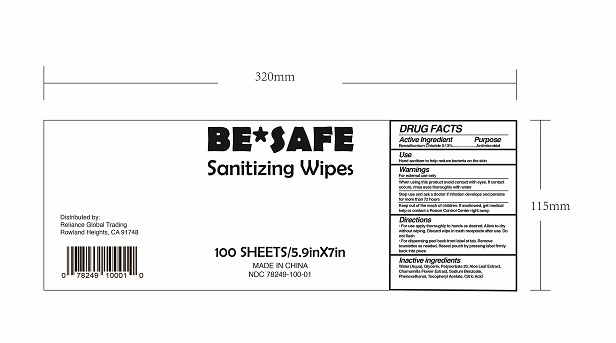 DRUG LABEL: Be Safe Sanitizing Wipes
NDC: 78249-100 | Form: CLOTH
Manufacturer: Reliance Global Trading
Category: otc | Type: HUMAN OTC DRUG LABEL
Date: 20200604

ACTIVE INGREDIENTS: BENZALKONIUM CHLORIDE 0.0013 mg/1 1
INACTIVE INGREDIENTS: WATER; GLYCERIN; POLYSORBATE 20; ALOE VERA LEAF; CHAMOMILE FLOWER OIL; SODIUM BENZOATE; PHENOXYETHANOL; TOCOPHEROL; CITRIC ACID ACETATE

Be Safe Sanitizing Wipes

Antiseptic

hand sanitizer to help reduce bacteria on skin

ACTIVE INGREDIENT

Benzalkonium Chloride 0.13%

INDICATIONS AND USAGE

to decrease bacteria on the skin

WARNINGS

For external hands only

KEEP OUT OF REACH OF CHILDREN

In case of accidental ingestion, seek professional assistance or contact a Poison Control Center right away.

INACTIVE INGREDIENT

water, glycerin, polysorbate 20, aloe leaf extract, chamomilla flower extract, sodium benzoate, phenoxethanol, tocopheryl acetate, citric acid

INSTRUCTIONS FOR USE

wipe hands thoroughly with product and allow to dry

keep out of eyes. In case of contact with eyes, flush thoroughly with water.